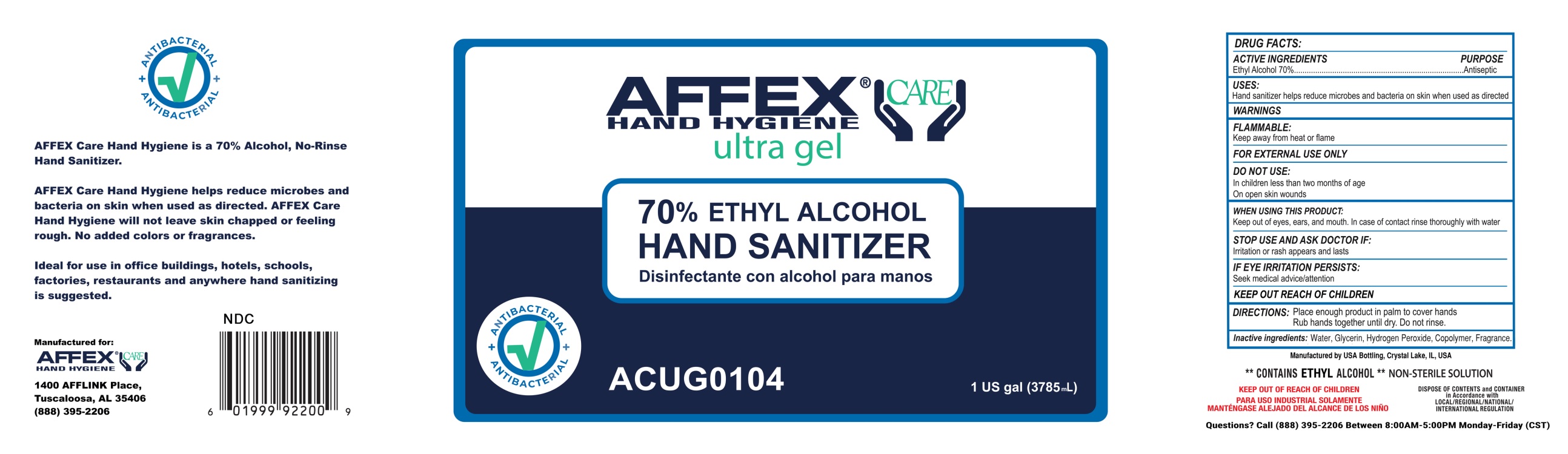 DRUG LABEL: AFFEX Care Ultra Hand Sanitizer
NDC: 79097-020 | Form: GEL
Manufacturer: Autotrol Corporation
Category: otc | Type: HUMAN OTC DRUG LABEL
Date: 20211206

ACTIVE INGREDIENTS: ALCOHOL 70 mL/100 mL
INACTIVE INGREDIENTS: ALOE; METHACRYLIC ACID - ETHYL ACRYLATE COPOLYMER (1:1) TYPE A; GLYCERIN; WATER; .ALPHA.-TOCOPHEROL ACETATE, DL-

27129 Hand Sanitizer

ACTIVE INGREDIENT

Ethyl Alcohol 70% v/v

PURPOSE

Antiseptic

INDICATIONS AND USAGE

Hand Sanitizer to help reduce bacteria that potentially can cause disease. For use when soap and water are not available.

WARNINGS

Flammable. Keep away from heat or flame

For external use only.

INSTRUCTIONS FOR USE

place enough product in your palm to thoroughly cover your hands
rub hands together briskly until dry
children under 6 years of age should be supervised when using this product

Keep out of reach of children. If swallowed, get medical help or contact a Poison Control Center right away.

OTHER SAFETY INFORMATION

Store between 15-30C (59-86F)Avoid freezing and excessive heat above 40C (104F)

DOSAGE AND ADMINISTRATION

Place enough product on hands to cover all surfaces. Rub hands together until dry.
Supervise children under 6 years of age when using this product to avoid swallowing.

When using this product do not use in or near the eyes. In case of contact, rinse eyes thoroughly with water.

Stop use and ask a physician if skin irritation or rash develops.

INACTIVE INGREDIENT

Water, Glycerin, Carbomer, Aloe, Tocopheryl Acetate

PACKAGE LABEL

3785 mL NDC: 79097-020-28